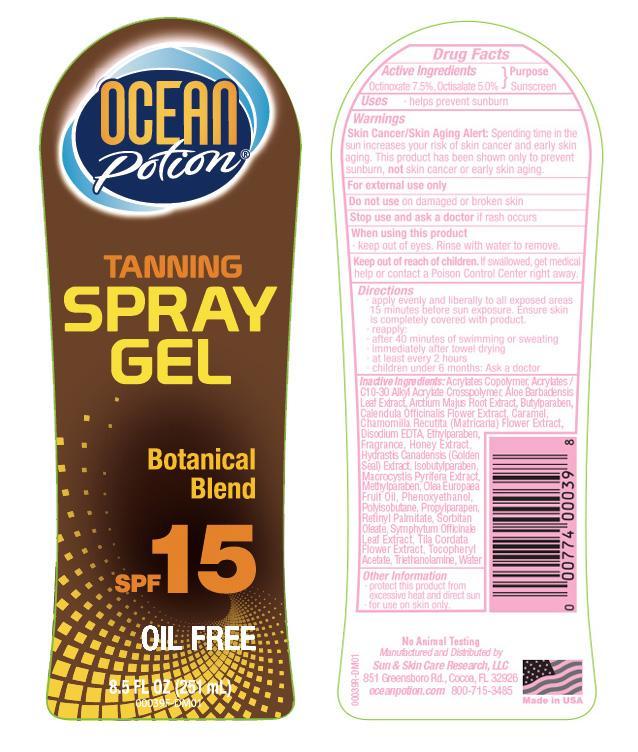 DRUG LABEL: OP Protective Gel 15
NDC: 62802-039 | Form: SPRAY
Manufacturer: Sun & Skin Care Research, LLC
Category: otc | Type: HUMAN OTC DRUG LABEL
Date: 20140718

ACTIVE INGREDIENTS: OCTINOXATE 7.5 g/100 g; OCTISALATE 5.0 g/100 g
INACTIVE INGREDIENTS: CARBOMER COPOLYMER TYPE A (ALLYL PENTAERYTHRITOL CROSSLINKED); ALOE VERA LEAF; VITAMIN A PALMITATE; ALPHA-TOCOPHEROL ACETATE; BUTYLPARABEN; EDETATE DISODIUM; ETHYLPARABEN; ISOBUTYLPARABEN; METHYLPARABEN; PHENOXYETHANOL; POLYISOBUTYLENE (2300 MW); HONEY; CALENDULA OFFICINALIS FLOWER; CHAMOMILE; PROPYLPARABEN; HYDRASTIS CANADENSIS WHOLE; MACROCYSTIS PYRIFERA; SYMPHYTUM OFFICINALE WHOLE; SORBITAN MONOOLEATE; TROLAMINE; WATER; CARAMEL; OLIVE OIL

DRUG FACTS

Active Ingredients

- Octinoxate 7.5%
- Octisalate 5.0%

Purpose

Sunscreen

Uses

- Helps prevent sunburn

Warnings

Skin Cancer / Skin Aging Alert: Spending time in the sun increases your risk of skin cancer and early skin aging. This product has been shown only to prevent sunburn, not skin cancer or early skin aging.

For external use only. Do not use on damaged or broken skin. Stop use and ask a doctor if rash occurs. When using this product keep out of eyes. Rinse with water to remove. Keep out of the reach of children. If swallowed, get medical help or call a poison control center right away.

Directions

- apply evenly and liberally to all exposed areas 15 minutes before sun exposure. Ensure skin is completely covered with product.
- reapply after 40 minutes of swimming or sweating, immediately after towel drying and at least every 2 hours
- children under 6 months: Ask a doctor

Other Information

- protect this product from excessive heat and direct sun
- for use on skin only
- avoid contact with fabric